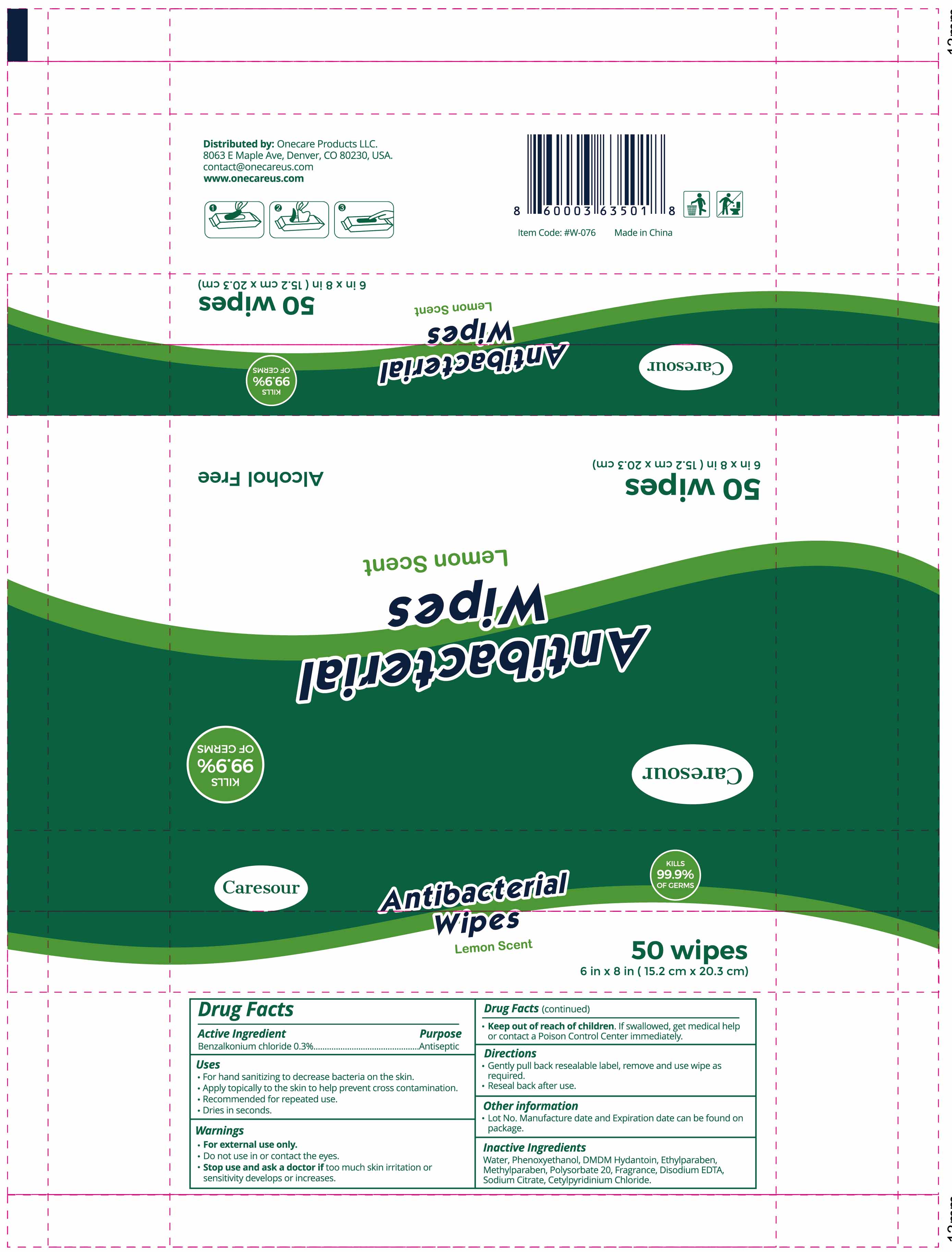 DRUG LABEL: Caresour Antibacterial Wipes Lemon Scented
NDC: 75513-002 | Form: SOLUTION
Manufacturer: Onecare Products LLC
Category: otc | Type: HUMAN OTC DRUG LABEL
Date: 20200615

ACTIVE INGREDIENTS: BENZALKONIUM CHLORIDE 9.6 mg/1 1
INACTIVE INGREDIENTS: WATER; PHENOXYETHANOL; DMDM HYDANTOIN; ETHYLPARABEN; METHYLPARABEN; SODIUM CITRATE; CETYLPYRIDINIUM CHLORIDE; POLYSORBATE 20; DISODIUM HEDTA

Caresour

Active Ingredient

Benzalkonium Chloride 0.3%

Purpose

Antiseptic

USE

For hand sanitizing to decrease bacteria on the skin.

Apply topically to the skin to help prevent cross contamination.
Recommended for repeated use.
Dries in seconds.

Warning

●For external use only.
Do not use in or contact the eyes.
●Stop use and ask a doctor if too much skin irritation or sensitivity develops or increases

●. Keep out of reach of children. If swallowed, get medical help or contact a Poison Control Center
immediately.

Directions

●Gentally pull back reusablelabel, remove and use wipe as required.
●Reseal back after use

Other Information

Lot No, Manufacture date, and Expiration date can be found on package

Inactive ingredients

Water, Phenoxyethanol, DMDM Hydantoin, Ethylparaben, Methylparaben, Polysorbate 20, Fragrance, Disodium EDTA, Sodium Citrate, Cetylpyridinium Chloride